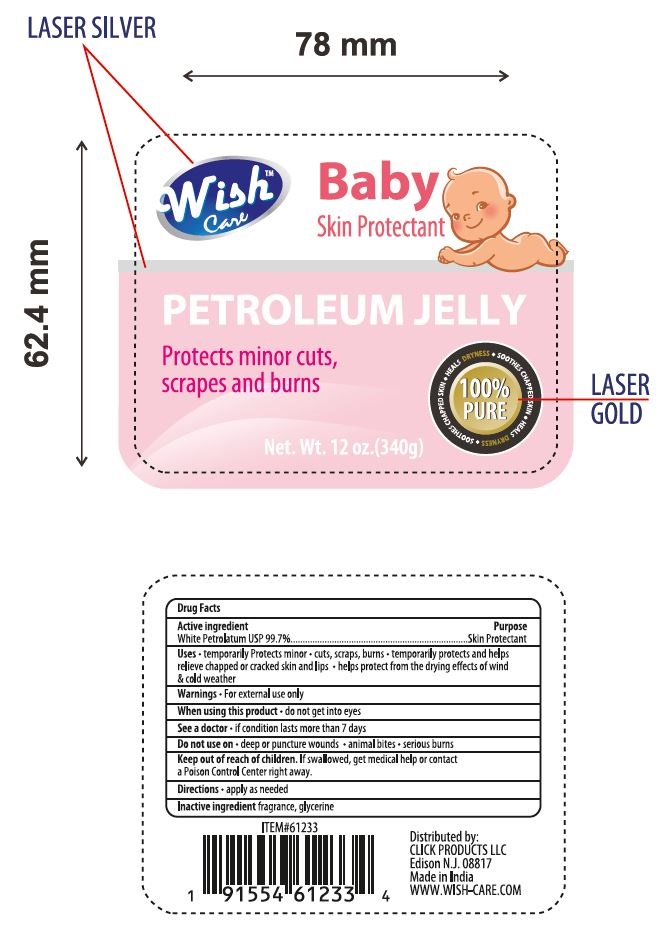 DRUG LABEL: Wish Care
NDC: 71611-006 | Form: CREAM
Manufacturer: Click Products LLC
Category: otc | Type: HUMAN OTC DRUG LABEL
Date: 20200318

ACTIVE INGREDIENTS: PETROLATUM 99.7 g/100 g
INACTIVE INGREDIENTS: GLYCERIN

ACTIVE INGREDIENT

White Petrolatum USP 99.7%

PURPOSE

Skin Protectant

DOSAGE AND ADMINISTRATION

Apply as needed

USES

Temporarily protects minor cuts, scrapes, burns.

Temporarily protects and helps relieve chapped or cracked skin and lips. helps protect from the drying effects of wind and cold weather.

KEEP OUT OF REACH OF CHILDREN. If swallowed, get medical help or contact a poison control center right away.

WARNINGS

For external use only

- When using this product, do not get into eyes
- See a doctor if condition lasts more than 7 days
- Do not use on deep or puncture wounds, animal bites, serious burns

INACTIVE INGREDIENT

Glycerine, fragrance